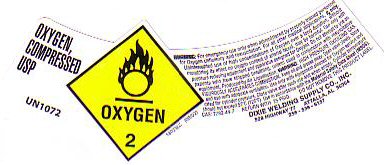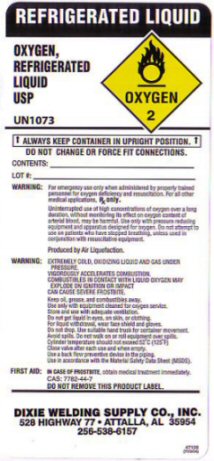 DRUG LABEL: OXYGEN
NDC: 50693-276 | Form: GAS
Manufacturer: Dixie Welding Supply Co, Inc.
Category: prescription | Type: HUMAN PRESCRIPTION DRUG LABEL
Date: 20220407

ACTIVE INGREDIENTS: OXYGEN 99.5 L/100 L

GENERAL WARNINGS AND PRECAUTIONS

FOR EMERGENCY USE ONLY WHEN ADMINISTERED BY PROPERLY TRAINED PERSONNEL FOR OXYGEN DEFICIENCY AND RESUSCITATION. FOR ALL OTHER MEDICAL APPLICATIONS Rx ONLY. UN-INTERRUPTED USE OF HIGH CONCENTRATIONS OF OXYGEN OVER A LONG DURATION WITHOUT MONITORING ITS EFFECT ON OXYGEN CONTENT OF ARTERIAL BLOOD MAY BE HARMFUL. USE ONLY WITH PRESSURE REDUCING EQUIPMENT AND APPARATUS DESIGNED FOR OXYGEN. DO NOT ATTEMPT TO USE ON PATIENTS WHO HAVE STOPPED BREATHING, UNLESS USED IN CONJUNCTION WITH RESUSCITATIVE EQUIPMENT.

WARNING: VIGOROUSLY ACCELERATED COMBUSTION. KEEP OIL GREASE AND COMBUSTIBLES AWAY. USE ONLY WITH EQUIPMENT CLEANED FOR OXYGEN SERVICE. STORE AND USE WITH ADEQUATE VENTILATION. DO NOT DROP. CYLINDER TEMPERATURE SHOULD NOT EXCEED 52 C (125 F) CLOSE VALVE AFTER EACH USE AND WHEN EMPTY. USE A BACKFLOW PREVENTATIVE DEVICE IN THE PIPING. USE IN ACCORDANCE WITH THE MATERIAL SAFETY DATA SHEET (MSDS) DO NOT REMOVE THIS PRODUCT LABEL.

OXYGEN COMPRESSED LABEL

OXYGEN COMPRESSED USP UN 1072 - OXYGEN - 2 - WARNING: HIGH PRESSURE OXIDIZING GAS VIGOROUSLY ACCELERATED COMBUSTION. CAS 7782-44-7 RETURN WITH 25 PSIG DO NOT REMOVE THIS PRODUCT LABEL

18033LC (08/02) PRODUCED BY AIR LIQUEFACTION. Rx ONLY

REFRIGERATED LIQUID LABEL

REFRIGERATED LIQUID - OXYGEN REFRIGERATED LIQUID USP - OXYGEN - 2 - UN 1073 ALWAYS KEEP CONTAINER IN UPRIGHT POSITION. DO NOT FORCE FIT CONNECTIONS CONTENTS ________________ LOT # _______________

PRODUCED BY AIR LIQUEFACTION Rx ONLY

WARNING: EXTREMELY COLD, OXIDIZING GAS AND LIQUID UNDER PRESSURE. COMBUSTIBLES IN CONTACT WITH LIQUID MAY EXPLODE ON IGNITION OR IMPACT. CAN CAUSE SEVERE FROSTBITE. DO NOT GET LIQUID IN EYES OR ON SKIN OR CLOTHING. FOR LIQUID WITHDRAWAL WEAR FACE SHIELD AND GLOVES. DO NOT DROP. USE SUITABLE HAND TRUCK FOR CONTAINER MOVEMENT. AVOID SPILLS. DO NOT WALK OR ROLL EQUIPMENT THROUGH SPILLS. IN CASE OF FROSTBITE OBTAIN MEDICAL TREATMENT IMMEDIATELY

CAS 7782-44-7

47136 (R10/04)